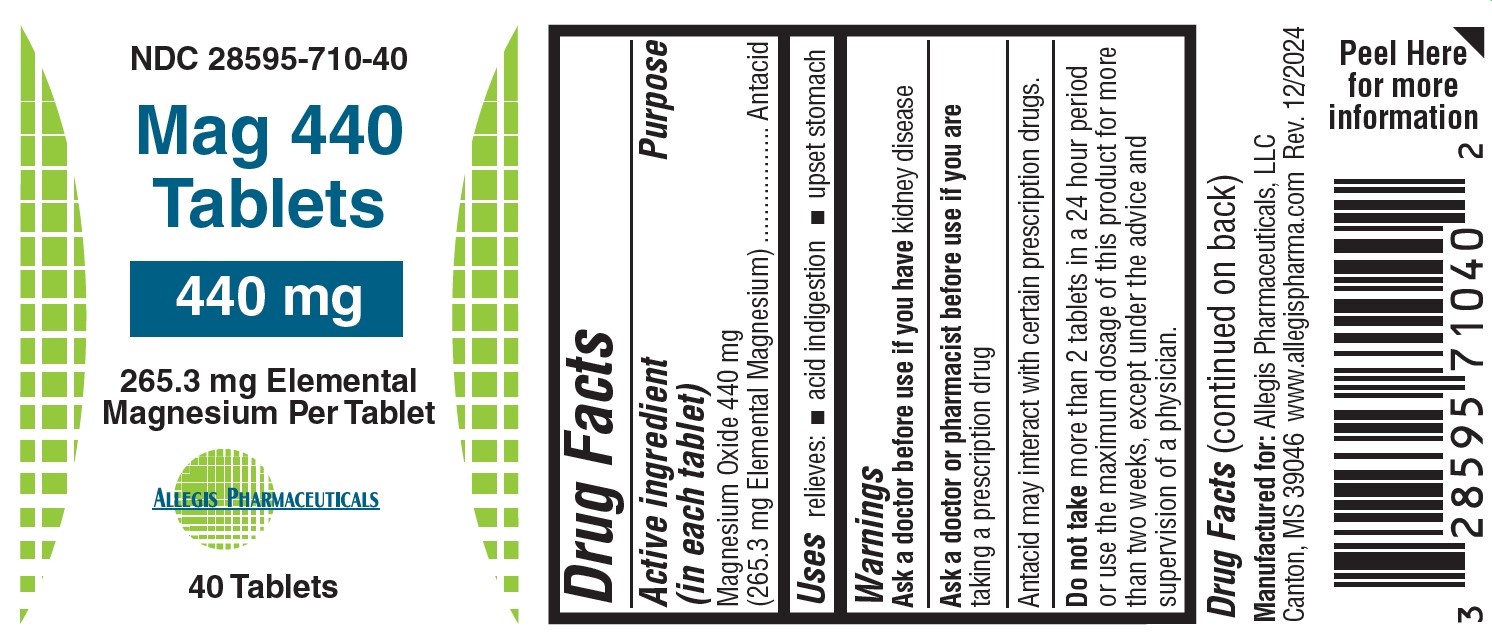 DRUG LABEL: Mag 440
NDC: 28595-710 | Form: TABLET
Manufacturer: Allegis Pharmaceuticals, LLC
Category: otc | Type: HUMAN OTC DRUG LABEL
Date: 20250417

ACTIVE INGREDIENTS: MAGNESIUM OXIDE 440 mg/1 1
INACTIVE INGREDIENTS: TITANIUM DIOXIDE; MAGNESIUM STEARATE; HYDROXYPROPYL METHYLCELLULOSE; POLYETHYLENE GLYCOL 1000000; CROSCARMELLOSE SODIUM; CELLULOSE, MICROCRYSTALLINE; STEARIC ACID

Mag 440

Drug Facts

Active Ingredient (in each tablet)..........................................................Purpose

Megnesium Oxide 440 mg (265.3 mg Elemental Magnesium).............Antacid

Uses

Relieves: Acid indigestion and upset stomach

Warnings

Ask a dcotor before use if you have kidney disease.

Ask a doctor or pharmacist before use if you are taking a presciption drug.

Antacid may interact with certian prescription drugs.

Do not take more than 2 tablets in a 24 hour period or use the maximum dosage of this product for more than two weeks, except under the advise and supervision of a physician.

If Pregnant or breast-feeding, ask a professional before use.

Keep out of the reach of children.

Directions

Antacid Directions: take 1 tablet trice a day or as directed by a Physician.

Magnesium Supplement Directions: Take 1 or 2 tablets day or as directed by a Physician.

Other Information

Magnesium content per tablet: 265.3 mg

Store at controlled room temperature 59 - 86 F (15 - 30 C)

Do not use if imprinted safety seal under cap is broken or missing.

Inactive ingredients

Croscarmellose Sodium, Microcrystalline Cellulose, Stearic Acid, Megnesium Stearate, Coating composition: Hydroxypropyl Methylcellulose (HPMC), Titanium Dioxide, PEG.

Questions? Comments?

Call 1-601-859-0038

How Supplied

Manufactured For: Allegis Pharmaceuticals, LLC
Canton, MS 39046
www.allegispharma.com

Rev 12/2024

Purpose

Purpose: Antacid